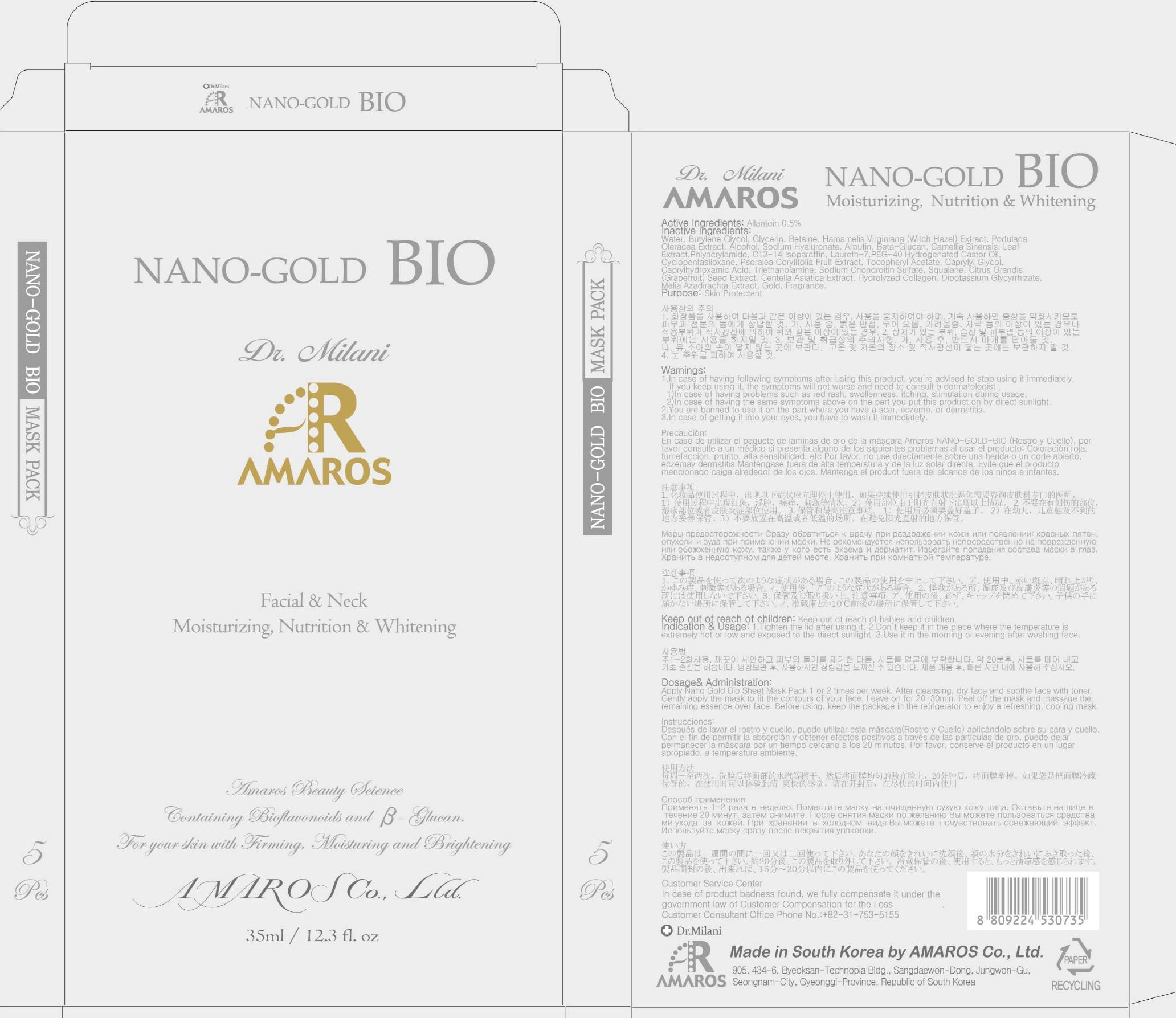 DRUG LABEL: Nano Gold Bio Mask Pack
NDC: 60899-020 | Form: PATCH
Manufacturer: AMAROS CO., LTD.
Category: otc | Type: HUMAN OTC DRUG LABEL
Date: 20190411

ACTIVE INGREDIENTS: Allantoin 0.17 mg/35 mL
INACTIVE INGREDIENTS: Water; Glycerin

ACTIVE INGREDIENT

Active Ingredient: Allantoin 0.5%

INACTIVE INGREDIENT

Inactive Ingredients: Water, Butylene Glycol, Glycerin, Betaine, Hamamelis Virginiana (Witch Hazel) Extract, Portulaca Oleracea Extract, Alcohol, Sodium Hyaluronate, Arbutin, Beta-Glucan, Camellia Sinensis Leaf Extract, Polyacrylamide, C13-14 Isoparaffin,Laureth-7, PEG-40 Hydrogenated Castor Oil, Cyclopentasiloxane, Psoralea Corylifolia Fruit Extract, Tocopheryl Acetate, Caprylyl Glycol, Caprylhydroxamic Acid, Triethanolamine, Sodium Chondroitin Sulfate, Squalane, Citrus Grandis (Grapefruit) Seed Extract, Centella Asiatica Extract, Hydrolyzed Collagen, Dipotassium Glycyrrhizate, Melia Azadirachta Extract, Gold, Fragrance.

PURPOSE

Purpose: Skin Protectant

WARNINGS

Warnings: 1. In case of having following symptoms after using this product, you're advised to stop using it immediately. If you keep using it, the symptoms will get worse and need to consult a dermatologist. 1) In case of having problems such as red rash, swollenness, itching, stimulation during usage. 2) In case of having the same symptoms above on the part you put this product on by direct sunlight. 2. You are banned to use it on the part where you have a scar, eczema, or dermatitis. 3. In case of getting it into your eyes, you have to wash it immediately.

Keep out of reach of children: Keep out of reach of babies and children

INDICATIONS AND USAGE

Indication and Usage: 1. Tighten the lid after using it. 2. Don't keep it in the place where the temperature is extremely hot or low and exposed to the direct sunlight. 3. Use it in the morning or evening after washing face.

Dosage and Administration: Apply Nano Gold Bio Sheet Mask Pack 1 or 2 times per week. After cleansing, dry face and soothe face with toner. Gently apply the mask to fit the contours of your face. Leave on for 20-30min. Peel off the mask and massage the remaining essence over face. Before using, keep the package in the refrigerator to enjoy a refreshing, cooling mask.